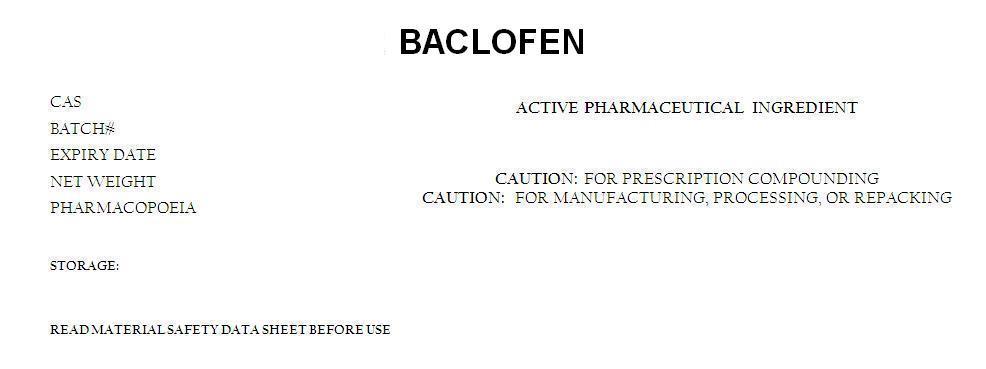 DRUG LABEL: BACLOFEN
NDC: 62448-134 | Form: POWDER
Manufacturer: BOSTON SYNTHETICS LIMITED
Category: other | Type: BULK INGREDIENT
Date: 20151201

ACTIVE INGREDIENTS: BACLOFEN 1 g/1 g

BACLOFEN